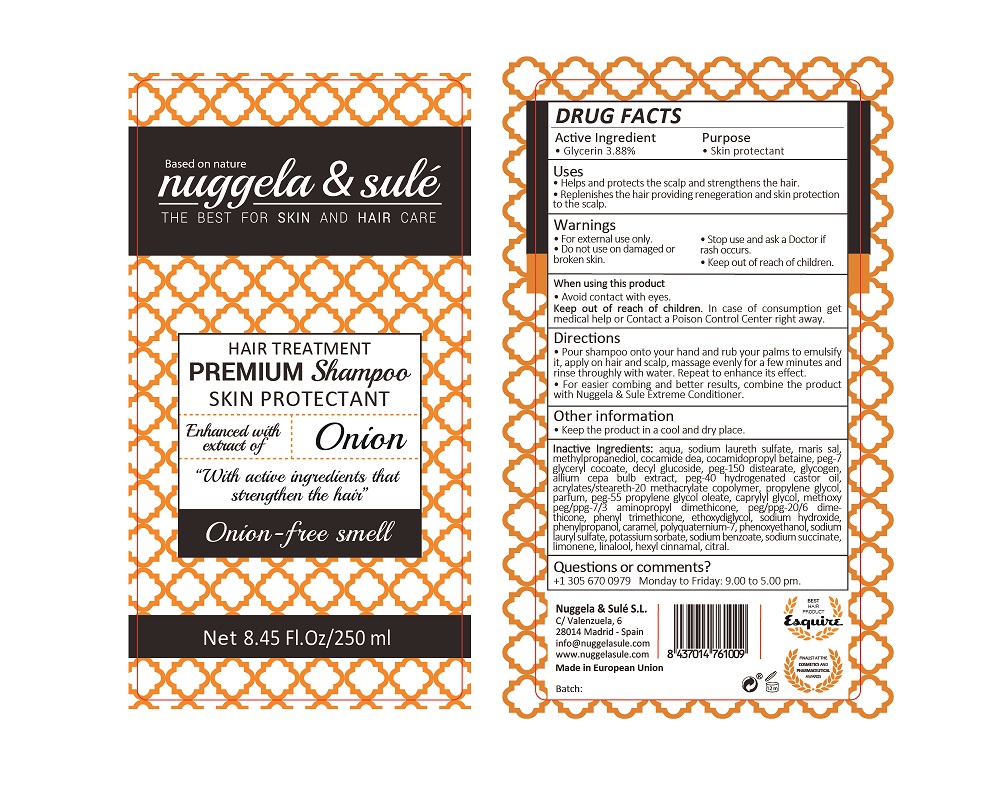 DRUG LABEL: HAIR TREATMENT PREMIUM
NDC: 71578-006 | Form: SHAMPOO
Manufacturer: NUGGELA & SULE SL
Category: otc | Type: HUMAN OTC DRUG LABEL
Date: 20200528

ACTIVE INGREDIENTS: GLYCERIN 3.88 mg/1 mL
INACTIVE INGREDIENTS: PEG/PPG-20/6 DIMETHICONE 0.5 mg/1 mL; PHENYL TRIMETHICONE 0.5 mg/1 mL; PHENYLPROPANOL 0.07 mg/1 mL; .ALPHA.-HEXYLCINNAMALDEHYDE 0.0001 mg/1 mL; SODIUM CHLORIDE 4 mg/1 mL; SODIUM LAURYL SULFATE 0.0112 mg/1 mL; POTASSIUM SORBATE 0.0025 mg/1 mL; METHOXY PEG/PPG-7/3 AMINOPROPYL DIMETHICONE 0.5 mg/1 mL; PEG-10 ACRYLATE 0.6 mg/1 mL; ETHYL ACRYLATE/METHACRYLIC ACID/STEARETH-20 METHACRYLATE COPOLYMER 0.84 mg/1 mL; CITRAL 0.001 mg/1 mL; ONION 0.02 mg/1 mL; SODIUM LAURETH SULFATE 8.91 mg/1 mL; COCO DIETHANOLAMIDE 2 mg/1 mL; DIETHYLENE GLYCOL MONOETHYL ETHER 0.3 mg/1 mL; CARAMEL 0.048 mg/1 mL; SODIUM SUCCINATE HEXAHYDRATE 0.01 mg/1 mL; SODIUM HYDROXIDE 0.08 mg/1 mL; DECYL GLUCOSIDE 1 mg/1 mL; PEG-150 DISTEARATE 1 mg/1 mL; PEG-7 GLYCERYL COCOATE 1.5 mg/1 mL; COCAMIDOPROPYL BETAINE 1.8 mg/1 mL; LINALOOL, (-)- 0.0001 mg/1 mL; WATER 100 mg/1 mL; PHENOXYETHANOL 0.015 mg/1 mL; POLYQUATERNIUM-7 (70/30 ACRYLAMIDE/DADMAC; 1600000 MW) 0.04 mg/1 mL; METHYLPROPANEDIOL 2.4 mg/1 mL; SODIUM BENZOATE 0.0025 mg/1 mL; PROPANEDIOL 0.825 mg/1 mL; LIMONENE, (+)- 0.01 mg/1 mL; CAPRYLYL GLYCOL 0.52 mg/1 mL; GLYCOGEN 0.05 mg/1 mL; PEG-40 CASTOR OIL 0.97 mg/1 mL

Hair treatment premium shampoo

ACTIVE INGREDIENTS PURPOSE

Glycerin 3.88 %.................... Skin Protectant

Warnings

For external use only.

Do not use on damaged or broken skin.

Stop use and ask a doctor if rash occurs.

Keep out of reach of children.

Whhen using this product do not get into eyes.

Children under 6 months: as a doctor.

WARNINGS

Stop use and ask a doctor if rash occurs

Children under 6 months: ask a doctor

Warnings

Keep out of reach of children

Questions or comments?

+ 305 670 0979 M-F 9:00 am to 5:00 pm

Other Information

. keep the product in a cool and dry place

Directions

- Pour shampoo unto your hand and rub your palms to emulsify it, apply on hair and scalp, massage evenly for a few minutes and rinse throughly with water. Repeat to enhance its effects
- For easier combining and better results, combine the product with Nuggela & Sule Extreme conditioner.

DOSAGE AND ADMINISTRATION

- Pour shampoo unto your hand and rub your palms to emulsify it, apply on hair and scalp, massage evenly for a few minutes and rinse throughly with water. Repeat to enhance its effects
- For easier combining and better results, combine the product with Nuggela & Sule Extreme conditioner.

Uses

- Helps and protects the scalp and strengthens the hair
- Replenish the hair providing regeneration and skin protection to the scalp.

Inactive Ingredients

AQUA, SODIUM LAURETH SULFATE, MARIS SAL, METHYLPROPANEDIOL, COCAMIDE DEA, COCAMIDOPROPYL BETAINE, PEG-7 GLYCERYL COCOATE, DECYL GLUCOSIDE, PEG-150 DISTEARATE, GLYCOGEN, ALLIUM CEPA BULB EXTRACT, PEG-40 HYDROGENATED CASTOR OIL, ACRYLATES/STEARETH-20 METHACRYLATE COPOLYMER, PROPYLENE GLYCOL, PARFUM, PEG-55 PROPYLENE GLYCOL OLEATE, CAPRYLYL GLYCOL, METHOXY PEG/PPG-7/3 AMINOPROPYL DIMETHICONE, PEG/PPG-20/6 DIMETHICONE, PHENYL TRIMETHICONE, ETHOXYDIGLYCOL, SODIUM HYDROXIDE, PHENYLPROPANOL, CARAMEL, POLYQUATERNIUM-7, PHENOXYETHANOL, SODIUM LAURYL SULFATE, POTASSIUM SORBATE, SODIUM BENZOATE, SODIUM SUCCINATE, LIMONENE, LINALOOL, HEXYL CINNAMAL, CITRAL

Uses

- Helps and protects the scalp and strengthens the hair
- Replenish the hair providing regeneration and skin protection to the scalp.